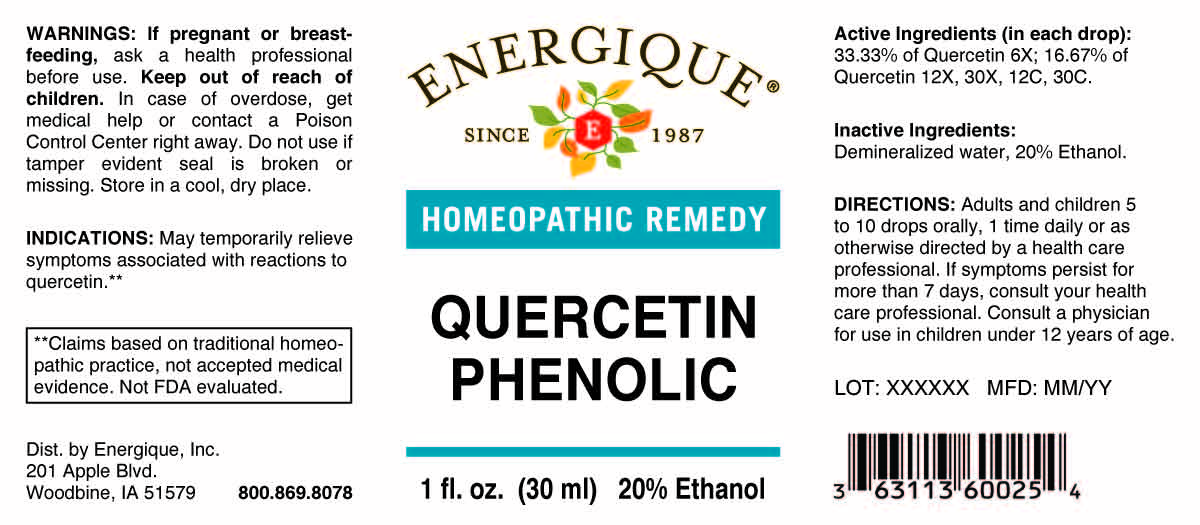 DRUG LABEL: Quercetin Phenolic
NDC: 44911-0013 | Form: LIQUID
Manufacturer: Energique, Inc.
Category: homeopathic | Type: HUMAN OTC DRUG LABEL
Date: 20251203

ACTIVE INGREDIENTS: QUERCETIN 6 [hp_X]/1 mL
INACTIVE INGREDIENTS: ALCOHOL; WATER

DRUG FACTS:

ACTIVE INGREDIENT:

(in each drop): 33.33% of Quercetin 6X; 16.67% of Quercetin 12X, 30X, 12C, 30C.

PURPOSE:

May temporarily relieve symptoms associated with reactions to quercetin.**

**Claims based on traditional homeopathic practice, not accepted medical evidence. Not FDA evaluated.

WARNINGS:

If pregnant or breast-feeding, ask a health professional before use.

Keep out of reach of children. In case of overdose, get medical help or contact a Poison Control Center right away.

Do not use if tamper evident seal is broken or missing.

Store in a cool, dry place.

KEEP OUT OF REACH OF CHILDREN:

In case of overdose, get medical help or contact a Poison Control Center right away.

DIRECTIONS:

Adults and children 5 to 10 drops orally, 1 time daily or as otherwise directed by a health care professional. If symptoms persist for more than 7 days, consult your health care professional. Consult a physician for use in children under 12 years of age.

INACTIVE INGREDIENTS:

Demineralized water, 20% Ethanol.

INDICATIONS:

May temporarily relieve symptoms associated with reactions to quercetin.**

**Claims based on traditional homeopathic practice, not accepted medical evidence. Not FDA evaluated.

QUESTIONS:

Dist. by Energique, Inc.

201 Apple Blvd.

Woodbine, IA 51579

800.869.8078

PACKAGE LABEL DISPLAY:

ENERGIQUE

SINCE 1987

HOMEOPATHIC REMEDY

QUERCETIN PHENOLIC

1 fl. oz. (30 ml)